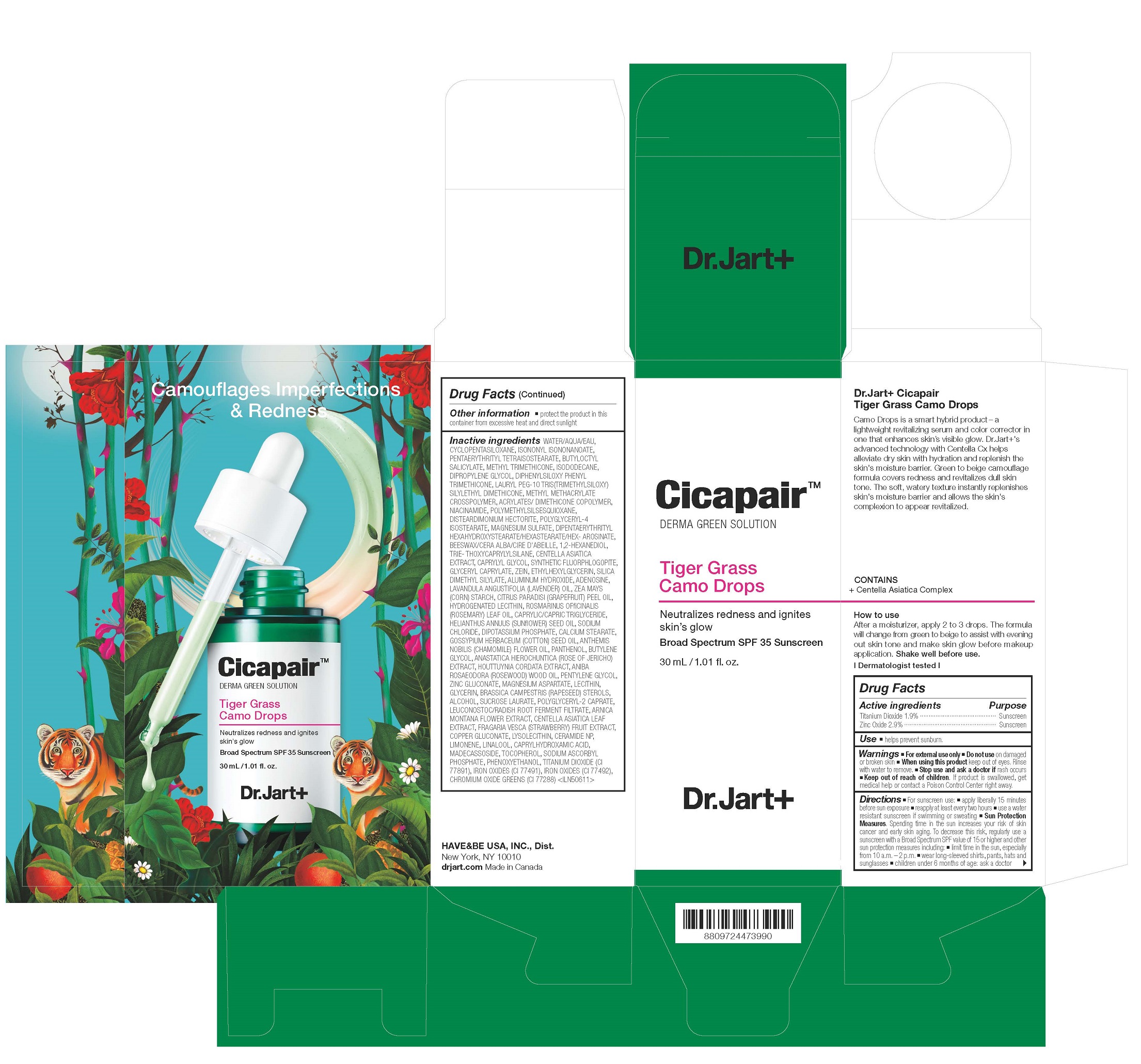 DRUG LABEL: Dr.Jart Cicapair Tiger Grass Camo Drops
NDC: 49404-305 | Form: CREAM
Manufacturer: Have & Be Co., Ltd.
Category: otc | Type: HUMAN OTC DRUG LABEL
Date: 20250206

ACTIVE INGREDIENTS: ZINC OXIDE 29 mg/1 mL; TITANIUM DIOXIDE 19 mg/1 mL
INACTIVE INGREDIENTS: MAGNESIUM POTASSIUM ALUMINOSILICATE FLUORIDE; POLYGLYCERYL-2 CAPRATE; CHROMIC OXIDE; YELLOW WAX; PANTHENOL; ROSEWOOD OIL; MADECASSOSIDE; PHENOXYETHANOL; LAVENDER OIL; LEUCONOSTOC/RADISH ROOT FERMENT FILTRATE; ARNICA MONTANA FLOWER; DIPHENYLSILOXY PHENYL TRIMETHICONE; ETHYLHEXYLGLYCERIN; CAPRYLHYDROXAMIC ACID; BUTYLENE GLYCOL; MAGNESIUM ASPARTATE; NIACINAMIDE; ALCOHOL; FERRIC OXIDE RED; WATER; ROSEMARY OIL; CHAMAEMELUM NOBILE FLOWER OIL; LECITHIN, SOYBEAN; RAPESEED STEROL; SUCROSE LAURATE; ISODODECANE; 1,2-HEXANEDIOL; ALUMINUM HYDROXIDE; ADENOSINE; ZINC GLUCONATE; DIPROPYLENE GLYCOL; PENTYLENE GLYCOL; GLYCERIN; LIMONENE, (+)-; SODIUM ASCORBYL PHOSPHATE; TRIETHOXYCAPRYLYLSILANE; CENTELLA ASIATICA TRITERPENOIDS; GRAPEFRUIT OIL; BUTYLOCTYL SALICYLATE; ZEIN; FRAGARIA VESCA FRUIT; FERRIC OXIDE YELLOW; CERAMIDE NP; LINALOOL, (+/-)-; TOCOPHEROL; CETYL DIGLYCERYL TRIS(TRIMETHYLSILOXY)SILYLETHYL DIMETHICONE (3500 MM2/S); MAGNESIUM SULFATE, UNSPECIFIED; SODIUM CHLORIDE; POTASSIUM PHOSPHATE, DIBASIC; LEVANT COTTON OIL; POLYGLYCERYL-4 ISOSTEARATE; LYSOPHOSPHATIDYLCHOLINE, SOYBEAN; PENTAERYTHRITYL TETRAISOSTEARATE; 2-ETHYLHEXYL ACRYLATE, METHACRYLATE, METHYL METHACRYLATE, OR BUTYL METHACRYLATE/HYDROXYPROPYL DIMETHICONE COPOLYMER (30000-300000 MW); GLYCERYL CAPRYLATE; STARCH, CORN; MEDIUM-CHAIN TRIGLYCERIDES; HOUTTUYNIA CORDATA FLOWERING TOP; HYDROGENATED SOYBEAN LECITHIN; SILICA DIMETHYL SILYLATE; CYCLOMETHICONE 5; POLY(METHYL METHACRYLATE; 450000 MW); DIPENTAERYTHRITYL HEXAHYDROXYSTEARATE; COPPER GLUCONATE; METHYL TRIMETHICONE; POLYMETHYLSILSESQUIOXANE (4.5 MICRONS); DISTEARDIMONIUM HECTORITE; CENTELLA ASIATICA LEAF; SUNFLOWER OIL; CAPRYLYL GLYCOL; ISONONYL ISONONANOATE; ANASTATICA HIEROCHUNTICA WHOLE; CALCIUM STEARATE

Dr.Jart Cicapair Tiger Grass Camo Drops

ACTIVE INGREDIENTS

Titanium Dioxide 1.9%
Zinc Oxide 2.9%

PURPOSE

Sunscreen

USE

helps prevent sunburn

WARNINGS

For external use only

Do not use

On damaged or broken skin

When using this product

keep out of eyes. Rinse with water to remove.

Stop use and ask a doctor if

rash occurs

Keep out of reach of children

If product is swallowed, get medical help or contact a Poison Control Center right away.

DIRECTIONS

■ For sunscreen use: ■ apply liberally 15 minutes before sun exposure ■ reapply at least every two hours ■ use a water resistant sunscreen if swimming or sweating ■ Sun Protection Measures. Spending time in the sun increases your risk of skin cancer and early skin aging. To decrease this risk, regularly use a sunscreen with a Broad Spectrum SPF value of 15 or higher and other sun protection measures including: ■ limit time in the sun, especially from 10 a.m. – 2 p.m. ■ wear long-sleeved shirts, pants, hats and sunglasses ■ children under 6 months of age: ask a doctor

INACTIVE INGREDIENTS

WATER/AQUA/EAU, CYCLOPENTASILOXANE, ISONONYL ISONONANOATE, PENTAERYTHRITYL TETRAISOSTEARATE, BUTYLOCTYL SALICYLATE, METHYL TRIMETHICONE, ISODODECANE, DIPROPYLENE GLYCOL, DIPHENYLSILOXY PHENYL TRIMETHICONE, LAURYL PEG-10 TRIS(TRIMETHYLSILOXY) SILYLETHYL DIMETHICONE, METHYL METHACRYLATE CROSSPOLYMER, ACRYLATES/ DIMETHICONE COPOLYMER, NIACINAMIDE, POLYMETHYLSILSESQUIOXANE, DISTEARDIMONIUM HECTORITE, POLYGLYCERYL-4 ISOSTEARATE, MAGNESIUM SULFATE, DIPENTAERYTHRITYL HEXAHYDROXYSTEARATE/HEXASTEARATE/HEX- AROSINATE, BEESWAX/CERA ALBA/CIRE D'ABEILLE, 1,2-HEXANEDIOL, TRIE- THOXYCAPRYLYLSILANE, CENTELLA ASIATICA EXTRACT, CAPRYLYL GLYCOL, SYNTHETIC FLUORPHLOGOPITE, GLYCERYL CAPRYLATE, ZEIN, ETHYLHEXYLGLYCERIN, SILICA DIMETHYL SILYLATE, ALUMINUM HYDROXIDE, ADENOSINE, LAVANDULA ANGUSTIFOLIA (LAVENDER) OIL, ZEA MAYS
(CORN) STARCH, CITRUS PARADISI (GRAPEFRUIT) PEEL OIL, HYDROGENATED LECITHIN, ROSMARINUS OFﬁCINALIS
(ROSEMARY) LEAF OIL, CAPRYLIC/CAPRIC TRIGLYCERIDE, HELIANTHUS ANNUUS (SUNﬂOWER) SEED OIL, SODIUM CHLORIDE, DIPOTASSIUM PHOSPHATE, CALCIUM STEARATE, GOSSYPIUM HERBACEUM (COTTON) SEED OIL, ANTHEMIS NOBILIS (CHAMOMILE) FLOWER OIL, PANTHENOL, BUTYLENE GLYCOL, ANASTATICA HIEROCHUNTICA (ROSE OF JERICHO) EXTRACT, HOUTTUYNIA CORDATA EXTRACT, ANIBA ROSAEODORA (ROSEWOOD) WOOD OIL, PENTYLENE GLYCOL, ZINC GLUCONATE, MAGNESIUM ASPARTATE, LECITHIN, GLYCERIN, BRASSICA CAMPESTRIS (RAPESEED) STEROLS, ALCOHOL, SUCROSE LAURATE, POLYGLYCERYL-2 CAPRATE, LEUCONOSTOC/RADISH ROOT FERMENT FILTRATE, ARNICA MONTANA FLOWER EXTRACT, CENTELLA ASIATICA LEAF EXTRACT, FRAGARIA VESCA (STRAWBERRY) FRUIT EXTRACT, COPPER GLUCONATE, LYSOLECITHIN, CERAMIDE NP, LIMONENE, LINALOOL, CAPRYLHYDROXAMIC ACID, MADECASSOSIDE, TOCOPHEROL, SODIUM ASCORBYL PHOSPHATE, PHENOXYETHANOL, TITANIUM DIOXIDE (CI 77891), IRON OXIDES (CI 77491), IRON OXIDES (CI 77492), CHROMIUM OXIDE GREENS (CI 77288) <ILN50611>

OTHER INFORMATION

protect the product in this container from excessive heat and direct sunlight

PACKAGE LABEL

Cicapair
DERMA GREEN SOLUTION

Tiger Grass
Camo Drops
Broad Spectrum SPF 35 Sunscreen

30 mL / 1.01 fl. oz.

Dr. Jart+